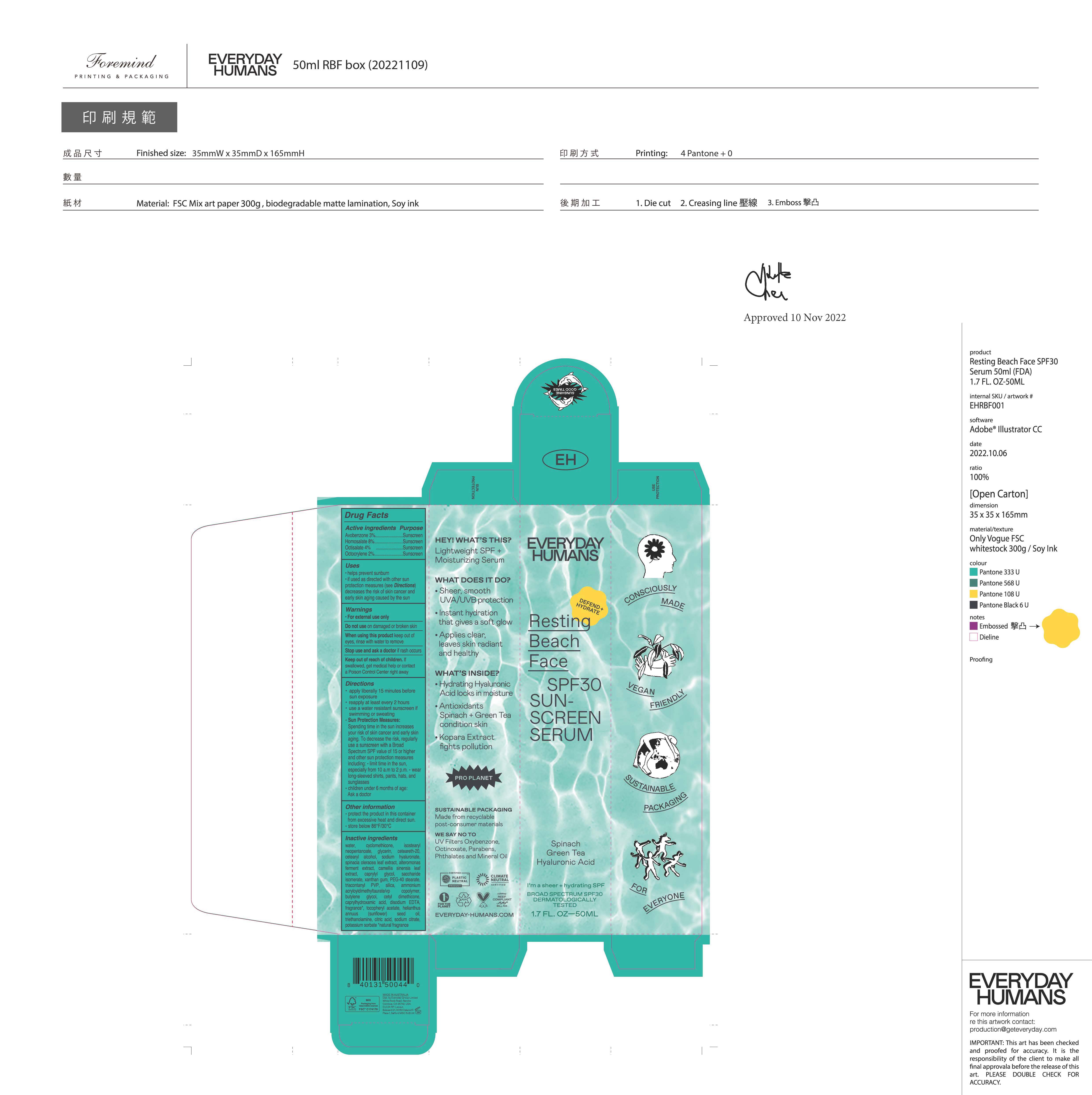 DRUG LABEL: Resting Beach Face Broad Spectrum SPF 30 Sunscreen Serum
NDC: 70157-031 | Form: CREAM
Manufacturer: Baxter Laboratories Pty. Ltd.
Category: otc | Type: HUMAN OTC DRUG LABEL
Date: 20250911

ACTIVE INGREDIENTS: OCTISALATE 4 g/100 mL; HOMOSALATE 8 g/100 mL; AVOBENZONE 3 g/100 mL; OCTOCRYLENE 2 g/100 mL
INACTIVE INGREDIENTS: EDETATE DISODIUM; SACCHARIDE ISOMERATE; .ALPHA.-TOCOPHEROL ACETATE; XANTHAN GUM; AMMONIUM ACRYLOYLDIMETHYLTAURATE/VP COPOLYMER; WATER; CAPRYLYL GLYCOL; CAPRYLHYDROXAMIC ACID; ISOSTEARYL NEOPENTANOATE; CYCLOMETHICONE; SPINACIA OLERACEA (SPINACH) LEAF POWDER; CAMELLIA SINENSIS LEAF; SODIUM HYALURONATE; HELIANTHUS ANNUUS (SUNFLOWER) SEED OIL; CETEARYL ALCOHOL; CETYL DIMETHICONE 45; SILICON DIOXIDE; POTASSIUM SORBATE; CETEARETH-20; ALTEROMONAS MACLEODII POLYSACCHARIDES; BUTYLENE GLYCOL; GLYCERIN; PEG-40 STEARATE; TRIACONTANYL PVP; SODIUM CITRATE; TRIETHANOLAMINE; CITRIC ACID

Resting Beach Face Broad Spectrum SPF 30 Sunscreen Serum

Active ingredients Purpose

Avobenzone 3%....Sunscreen

Homosalate 8%.....Sunscreen

Octisalate 4%......Sunscreen

Octocrylene 2%...Sunscreen

Uses

- Helps prevent sunburn
- If used as directed with other sun protection measures (see Directions), decreases the risk of skin cancer and early skin aging caused by the sun.

Keep out of reach of children. If swallowed, get medical help or contact a Poison Control Center right away.

Stop use and ask a doctor if rash occurs.

Warnings

- For external use only
- Do not use on damaged or broken skin
- When using this product, keep out of eyes, rinse with water to remove.

Directions

- Apply liberally 15 minutes before sun exposure
- Reapply at least every 2 hours
- use a water resistant sunscreen if swimming or sweating
- Sun Protection Measures: Spending time in the sun increases your risk of skin cancer and early skin aging. To decrease this risk, regularly use a sunscreen with a Broad Spectrum SPF value of 15 or higher and other sub and other sun protection measures including:
- Limit time in the sun, especially from 10 a.m.- 2 p.m.
- Wear long-sleeved shirts, pants, hats and sunglasses
- Children under 6 months: Ask a doctor

INACTIVE INGREDIENT

water, cyclomethicone, isostearyl neopentanoate, glycerin, ceteareth-20, cetearyl alcohol, sodium hyaluronate, spinacia oleracea leaf extract, alteromonas ferment extract, camellia sinensis leaf extract, caprylyl glycol, saccharide isomerate, xanthan gum, PEG-40 stearate, triacontanyl PVP, silica, ammonium acryloyldimethyltaurate/vp copolymer, butylene glycol, cetyl dimethicone, caprylhydroxamic acid, disodium EDTA, fragrance, tocopheryl acetate, helianthus annuus (sunflower) seed oil, triethanolamine, citric acid, sodium citrate, potassium sorbate

PACKAGE LABEL

Everyday Humans

Resting Beach face

SPF 30

Sun-screen Serum

Spinach

Green Tea

Hyaluronic Acid

I'm a sheer + hydrating SPF

Broad Spectrum SPF 30

Dermatologically testing

1.7 FL. OZ- 50ML